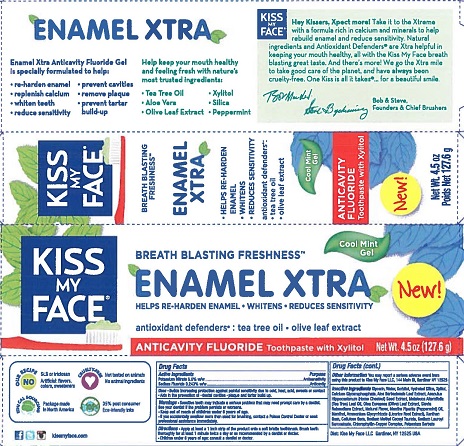 DRUG LABEL: Kiss My Face
NDC: 65364-403 | Form: GEL, DENTIFRICE
Manufacturer: Kiss My Face, LLC
Category: otc | Type: HUMAN OTC DRUG LABEL
Date: 20190220

ACTIVE INGREDIENTS: POTASSIUM NITRATE 5 g/100 g; SODIUM FLUORIDE 0.243 g/100 g
INACTIVE INGREDIENTS: CALCIUM GLYCEROPHOSPHATE; WATER; SODIUM LAURYL SARCOSINATE; SORBITOL; AESCULUS HIPPOCASTANUM SEED OIL; TEA TREE OIL; GLYCERIN; XANTHAN GUM; HYDRATED SILICA; OLEA EUROPAEA LEAF; SODIUM METHYL COCOYL TAURATE; ALOE VERA LEAF; MENTHOL; POTASSIUM SORBATE; XYLITOL; SODIUM COPPER CHLOROPHYLLIN; CARBOXYMETHYLCELLULOSE SODIUM, UNSPECIFIED FORM; STEVIA REBAUDIUNA LEAF; MENTHA PIPERITA; AMMONIUM GLYCYRRHIZATE

Kiss My Face Enamel Extra Cool Mint Gel Toothpaste

Drug Facts

Active ingredient

Potassium Nitrate 5.0% w/w

Sodium Fluoride 0.243% w/w

Purpose

Antihypersensitivity

Anticavity

Uses

- Builds increasing protection against painful due to cold, heat, acids, sweets or contact.
- Aids in the prevention of plaque and tarter build-up.

Warnings

- Sensitive teeth may indicate a serious problem that may need prompt care by a dentist. See your dentist if the problem persists or worsens.

- Keep out of reach of children under 6 years of age
- If you accidentally swallow more than used for brushing, contact a Poison Control Center or seek professional assistance immediately.

Directions

- Apply at least a 1 inch strip of the product onto a soft bristle toothbrush. Brush teeth thoroughly for at least one minute, preferably after each meal or at least twice a day or as recommended by a dentist or doctor.
- Children under 6 years of age: consult a dentist or doctor.

Other information

You may report a serious adverse event from using this product to Kiss My Face LLC, 144 Main St, Gardiner NY 12525.

INACTIVE INGREDIENT

Inactive ingredients Glycerin, Water, Sorbitol, Hydrated Silica, Xylitol, Calcium Glycerophosphate, Aloe Barbadensis (Aloe Vera) Leaf Extract*, Aesculus Hippocastanum (Horse Chestnut) Seed Extract, Melaleuca Alternifolia (Tea Tree) Leaf Oil, Olea Europaea (Olive) Leaf Extract, Stevia Rebaudiana Extract, Natural Flavor, Mentha Piperita (Peppermint) Oil, Menthol, Ammonium Glycyrrhizate (Licorice) Root Extract, Xanthan Gum, Cellulose Gum, Sodium Methyl Cocoyl Taurate, Sodium Lauroyl Saracosinate, Chlorophyllin-Copper Complex, Potassium Sorbate

Dist: Kiss My Face LLC

Gardiner, NY 12525 USA

PACKAGE LABEL

KISS MY FACE

BREATH BLASTING FRESHNESS

ENAMEL EXTRA

ANTICAVITY FLUORIDE Toothpaste with Xylitol

Cool Mint Gel

HELPS REHARDEN ENAMEL • WHITENS • REDUCES SENSITIVITY

antioxidant defenders™: tea tree oil • olive leaf extract

Net Wt. 4.5 oz (127.6 g)